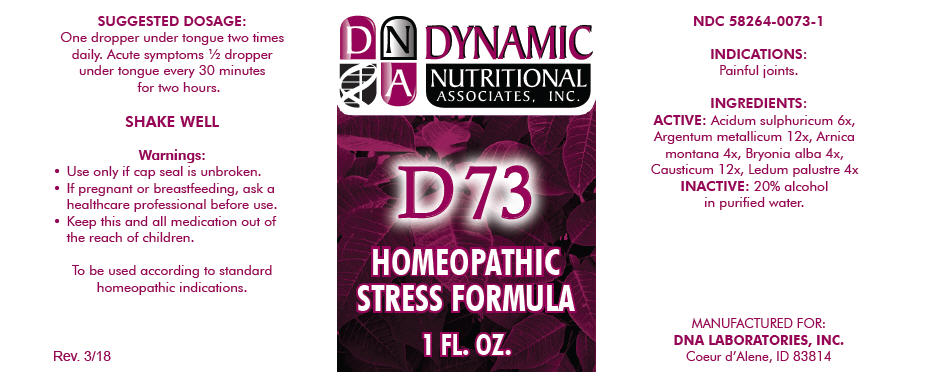 DRUG LABEL: D-73
NDC: 58264-0073 | Form: SOLUTION
Manufacturer: DNA Labs, Inc.
Category: homeopathic | Type: HUMAN OTC DRUG LABEL
Date: 20250113

ACTIVE INGREDIENTS: SULFURIC ACID 6 [hp_X]/1 mL; SILVER 12 [hp_X]/1 mL; ARNICA MONTANA 4 [hp_X]/1 mL; BRYONIA ALBA ROOT 4 [hp_X]/1 mL; CAUSTICUM 12 [hp_X]/1 mL; RHODODENDRON TOMENTOSUM LEAFY TWIG 4 [hp_X]/1 mL
INACTIVE INGREDIENTS: WATER; ALCOHOL

D-73

NDC 58264-0073-1

INDICATIONS

PURPOSE

Painful joints.

INGREDIENTS

ACTIVE

Acidum sulphuricum 6x, Argentum metallicum 12x, Arnica montana 4x, Bryonia alba 4x, Causticum 12x, Ledum palustre 4x

INACTIVE

20% alcohol in purified water.

SUGGESTED DOSAGE

One dropper under tongue two times daily. Acute symptoms ½ dropper under tongue every 30 minutes for two hours.

STORAGE AND HANDLING

SHAKE WELL

Warnings

- Use only if cap seal is unbroken.

PREGNANCY OR BREAST FEEDING

- If pregnant or breastfeeding, ask a healthcare professional before use.

KEEP OUT OF REACH OF CHILDREN

- Keep this and all medication out of the reach of children.

To be used according to standard homeopathic indications.

PRINCIPAL DISPLAY PANEL - 1 FL. OZ. Bottle Label

DYNAMIC
NUTRITIONAL
ASSOCIATES, INC.

D 73

HOMEOPATHIC
STRESS FORMULA

1 FL. OZ.